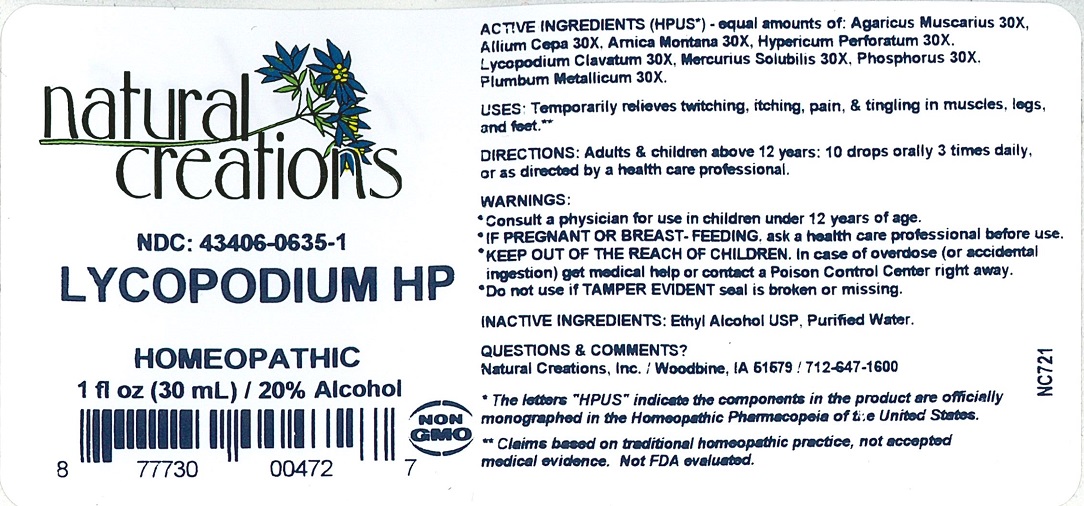 DRUG LABEL: LYCOPODIUM HP
NDC: 43406-0635 | Form: LIQUID
Manufacturer: Natural Creations, Inc
Category: homeopathic | Type: HUMAN OTC DRUG LABEL
Date: 20251216

ACTIVE INGREDIENTS: AMANITA MUSCARIA FRUITING BODY 30 [hp_X]/1 mL; ONION 30 [hp_X]/1 mL; ARNICA MONTANA 30 [hp_X]/1 mL; HYPERICUM PERFORATUM 30 [hp_X]/1 mL; LYCOPODIUM CLAVATUM SPORE 30 [hp_X]/1 mL; MERCURIUS SOLUBILIS 30 [hp_X]/1 mL; PHOSPHORUS 30 [hp_X]/1 mL; LEAD 30 [hp_X]/1 mL
INACTIVE INGREDIENTS: ALCOHOL; WATER

LYCOPODIUM HP

ACTIVE INGREDIENT

ACTIVE INGREDIENTS (HPUS*) - equal amounts of: Agaricus Muscarius 30X, Allium Cepa 30X, Arnica Montana 30X, Hypericum Perforatum 30X, Lycopodium Clavatum 30X, Mercurius Solubilis 30X, Phosphorus 30X, Plumbum Metallicum 30X.

PURPOSE

USES: Temporarily relieves twitching, itching, pain, & tingling in muscles, legs, and feet.**

INDICATIONS AND USAGE

USES: Temporarily relieves twitching, itching, pain, & tingling in muscles, legs, and feet.**

DOSAGE AND ADMINISTRATION

DIRECTIONS: Adults & children above 12 years: 10 drops orally 3 times daily, or as directed by a health care professional.

KEEP OUT OF REACH OF CHILDREN

KEEP OUT OF THE REACH OF CHILDREN. In case of overdose (or accidental ingestion) get medical help or contact a Poison Control Center right away.

WARNINGS:

- Consult a physician for use in children under 12 years of age.
- IF PREGNANT OR BREAST-FEEDING, ask a health care professional before use.
- KEEP OUT OF THE REACH OF CHILDREN. In case of overdose (or accidental ingestion) get medical help or contact a Poison Control Center right away.
- Do not use if TAMPER EVIDENT seal is broken or missing.

INACTIVE INGREDIENTS: Purified Water, Ethyl Alcohol USP.

QUESTIONS & COMMENTS?

Natural Creations, Inc. / Woodbine, IA 5159 / 712-647-1600

REFERENCES

*The letters "HPUS" indicate the component in this product are officially monographed in the Homeopathic Pharmacopeia of the United States.

**Claims based on tradtional homeopathic practice, not accepted medical evidence. Not FDA evaluated.

PACKAGE LABEL

NDC: 43406-0635-1

LYCOPODIUM HP

HOMEOPATHIC

1 fl oz (30 mL) / 20% Alcohol